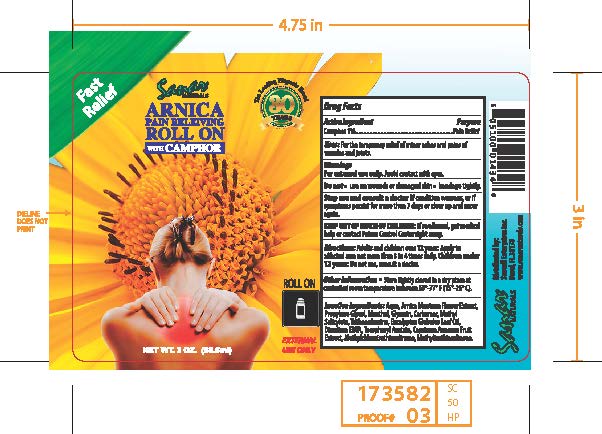 DRUG LABEL: Sanar Naturals Arnica Pain Releiving Roll On with Camphor
NDC: 73386-148 | Form: LIQUID
Manufacturer: Sanvall Enterprises, Inc
Category: otc | Type: HUMAN OTC DRUG LABEL
Date: 20241031

ACTIVE INGREDIENTS: CAMPHOR (SYNTHETIC) 1 mg/1 g
INACTIVE INGREDIENTS: METHYL SALICYLATE; EUCALYPTUS GLOBULUS LEAF; GLYCERIN; TROLAMINE; METHYLCHLOROISOTHIAZOLINONE; METHYLISOTHIAZOLINONE; CAPSICUM FRUTESCENS WHOLE; .ALPHA.-TOCOPHEROL ACETATE, D-; WATER; ARNICA MONTANA FLOWER; PROPYLENE GLYCOL; MENTHOL; CARBOMER 980; EDETATE DISODIUM ANHYDROUS

Sanar Naturals Arnica Pain Releiving Roll On with Camphor

Active ingredient

Camphor 1%

Purpose

Pain Relief

Uses

For the temporary relief of minor aches and pains of muscles joints

Warnings

For external use only

Avoid contact with eyes.

Do not

use on wounds or damaged skin

bandage tightly

Stop use and ask a doctor if

condition worsens, or if symptoms persist for more than 7 days or clear up and occur again.

Keep out of reach of children.

is swallowed, get medical help or contact Poison Control Center right away

Directions

- Adults and children over 12 years: Apply to affected area no more than 3 to 4 times daily.
- Children under 12 years: Do not use, consult a doctor.

Other Information

Store tightly closed in a dry place at controlled room temperature between 59-77 F (15-25 C)

Inactive ingredients

Aqua, Arnica Montana Flowe Extract, Propylene Glycol, Menthol, Glycerin, Carbomer, Methyl Salicylate, Ththanolamine, Eucalyptus Globulus Leaf Oil, Disodium EDTA, Tocopheryl Acetate, Capsicum Annum Fruit Extract, Methylchloroisothiazolinone, Methylisothiazolinone.